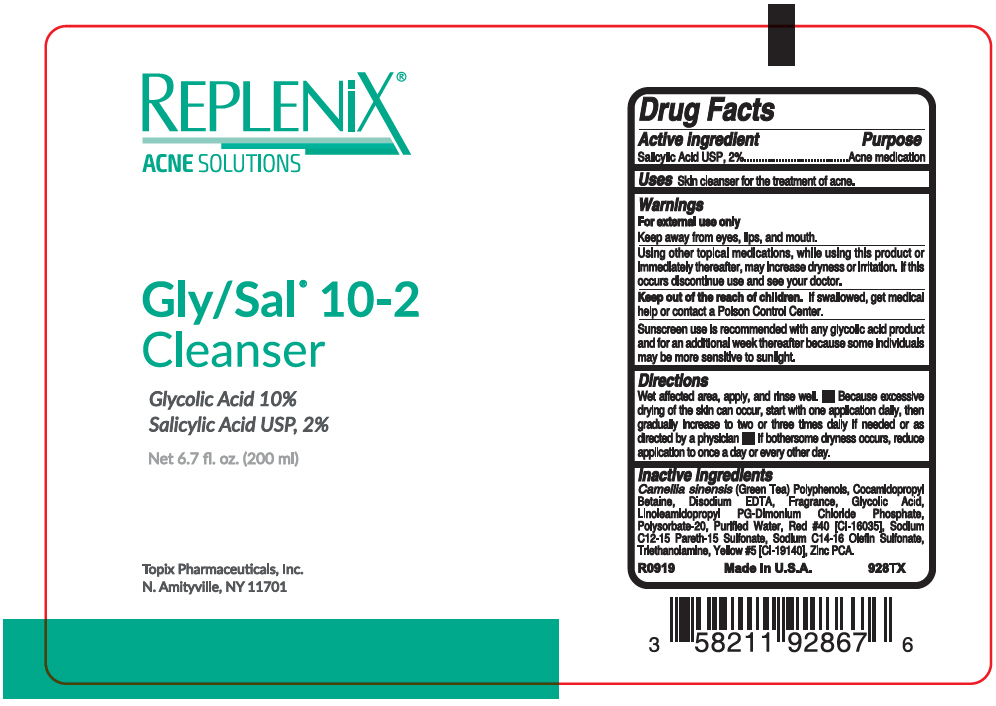 DRUG LABEL: Replenix Gly-Sal 10-2
NDC: 51326-928 | Form: LIQUID
Manufacturer: Topiderm, Inc.
Category: otc | Type: HUMAN OTC DRUG LABEL
Date: 20240802

ACTIVE INGREDIENTS: SALICYLIC ACID 20 mg/1 mL
INACTIVE INGREDIENTS: GREEN TEA LEAF; COCAMIDOPROPYL BETAINE; EDETATE CALCIUM DISODIUM; GLYCOLIC ACID; LINOLEAMIDOPROPYL PROPYLENE GLYCOL-DIMONIUM CHLORIDE PHOSPHATE; POLYSORBATE 20; WATER; FD&C RED NO. 40; SODIUM C12-15 ALKETH-15 SULFONATE; SODIUM C14-16 OLEFIN SULFONATE; TROLAMINE

Replenix® Gly-Sal 10-2
cleanser

Drug Facts

Active ingredient

Salicylic Acid USP, 2%

Purpose

Acne medication

Uses

Skin cleanser for the treatment of acne.

Warnings

For external use only

Keep away from eyes, lips, and mouth.

Using other topical medications, while using this product or immediately thereafter, may increase dryness or irritation. If this occurs discontinue use and see your doctor.

KEEP OUT OF REACH OF CHILDREN

Keep out of the reach of children. If swallowed, get medical help or contact a Poison Control Center.

Sunscreen use is recommended with any glycolic acid product and for an additional week thereafter because some individuals may be more sensitive to sunlight.

Directions

Wet affected area, apply, and rinse well.

- Because excessive drying of the skin can occur, start with one application daily, then gradually increase to two or three times daily if needed or as directed by a physician
- If bothersome dryness occurs, reduce application to once a day or every other day.

Inactive ingredients

Camellia sinensis (Green Tea) Polyphenols, Cocamidopropyl Betaine, Disodium EDTA, Fragrance, Glycolic Acid, Linoleamidopropyl PG-Dimonium Chloride Phosphate, Polysorbate-20, Purified Water, Red #40 [CI-16035], Sodium C12-15 Pareth-15 Sulfonate, Sodium C14-16 Olefin Sulfonate, Triethanolamine, Yellow #5 [CI-19140], Zinc PCA.

PRINCIPAL DISPLAY PANEL - 200 ml Bottle Label

REPLENiX®
ACNE SOLUTIONS

Gly/Sal® 10-2
Cleanser

Glycolic Acid 10%
Salicylic Acid USP, 2%

Net 6.7 fl. oz. (200 ml)

Topix Pharmaceuticals, Inc.
N. Amityville, NY 11701